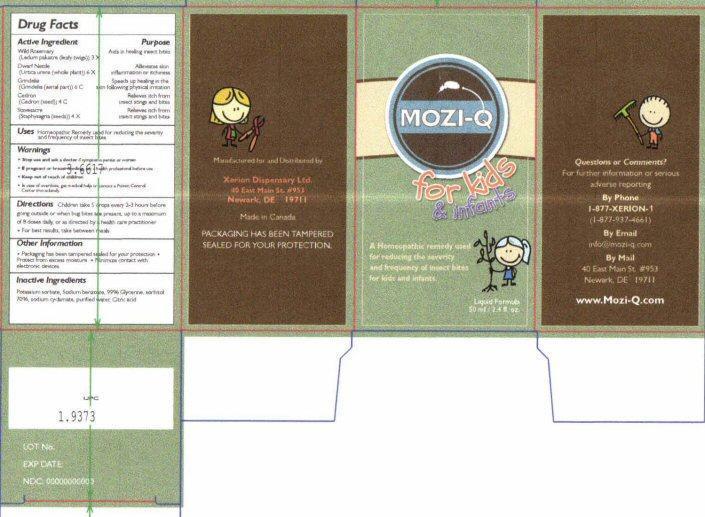 DRUG LABEL: MOZI-Qfor kids and infa
NDC: 53590-102 | Form: LIQUID
Manufacturer: Xerion Dispensary Ltd.
Category: homeopathic | Type: HUMAN OTC DRUG LABEL
Date: 20231217

ACTIVE INGREDIENTS: LEDUM PALUSTRE TWIG 3 [hp_X]/1 mL; URTICA URENS 6 [hp_X]/1 mL; GRINDELIA HIRSUTULA FLOWERING TOP 6 [hp_C]/1 mL; SIMABA CEDRON SEED 4 [hp_C]/1 mL; DELPHINIUM STAPHISAGRIA SEED 4 [hp_X]/1 mL
INACTIVE INGREDIENTS: POTASSIUM SORBATE; SODIUM BENZOATE; GLYCERIN; SORBITOL; SODIUM CYCLAMATE; WATER; CITRIC ACID MONOHYDRATE

Drug Facts Active Ingredients

Wild Rosemary (Ledum palustre (leafy twigs)) 3 X
Dwarf Nettle (Urtica urens (whole plant)) 6 X
Grindelia (Grindelia (aerial part)) 6 C
Cedron (Cedron (seed)) 4 C
Stavesacre (Staphysagria (seeds)) 4 X

Purpose

Aids in healing insect bites
Alleviates skin inflammation or itchiness
Speeds up healing in the skin following physical irritation
Relieves itch from insect stings and bites

Warnings Keep out of reach of children

Keep out of reach of children

Uses

Homeopathic Remedy used for reducing the severity and frequency of insect bites

Warnings

- Stop use and ask a doctor if symptoms persist or worsen
- If pregnant or breast-feeding ask a health professional before use
- In case of overdose, get medical help or contact a Poison Control Center immediately

Directions

Children take 5 drops every 2-3 hours before going outside or when bug bites are present, up to a maxium of 8 doses daily, or as directed by a health care practitioner

- For best results, take between meals

Other Information

- Packaging has been tampered sealed for your protection
- Protect from excessive moisture
- Minimize contact with electronic devices

Inactive Ingredients

Potassium sorbate, Sodium benzoate, 99% Glycerine, sorbitol 70%, sodium cyclamate, purified water, citric acid

Product Label MOZI-Q for kids & infants

MOZI-Q for kids and infants

A Homeopathic remedy used for reducing the severity and frequency of insect bites for kids and infants

Liquid Formula 50 ml / 2.4 fl. oz.

Questions or Comments?

For further information or serious adverse reporting

By Phone 1-877-XERION-1 (1-877-937-4661)

By Email info@mozi-q.com

By Mail 40 East Main St # 953 Newark, DE 19711

www.Mozi-Q.com

Manufactured for and Distributed by

Xerion Dispensary Ltd.

40 East Main St #953

Newark, DE 19711

Made in Canada

PACKAGING HAS BEEN TAMPERED SEALED FOR YOUR PROTECTION

LOT No.

EXP DATE:

NDC 00000000000